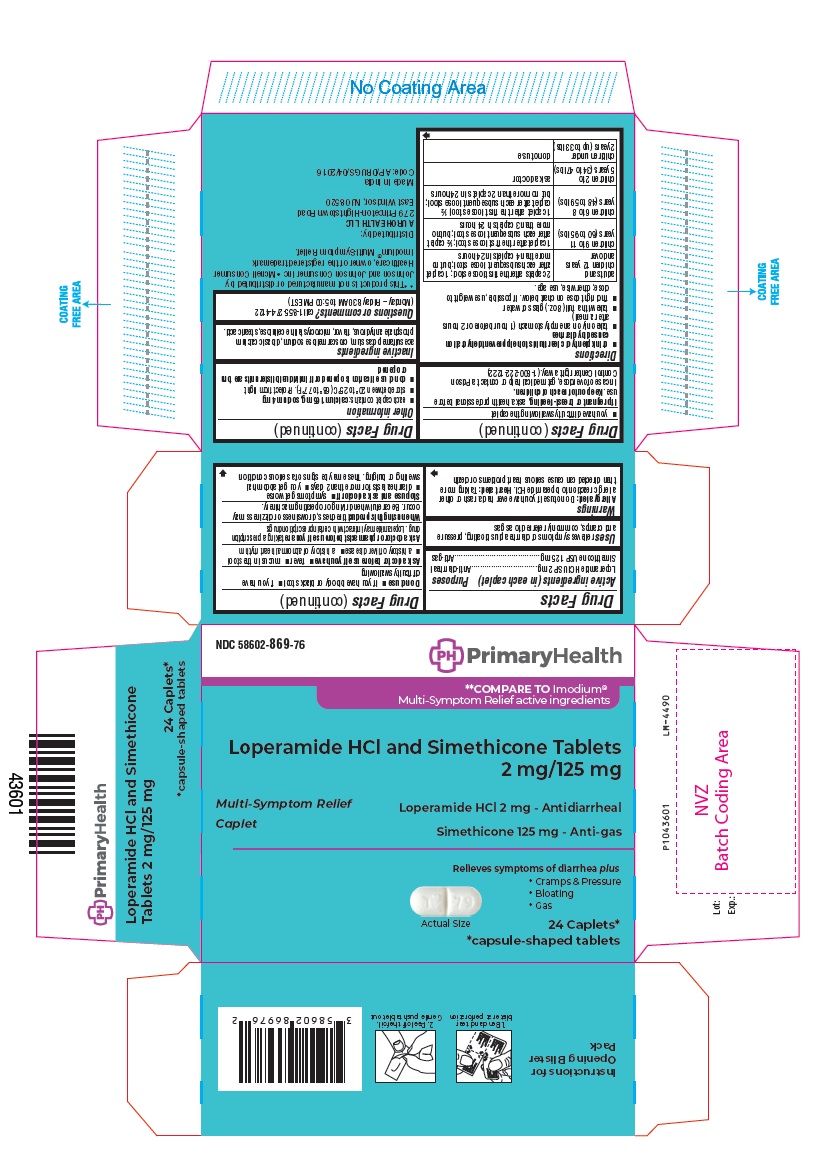 DRUG LABEL: Loperamide Hydrochloride and Simethicone
NDC: 58602-869 | Form: TABLET
Manufacturer: Aurohealth LLC
Category: otc | Type: Human OTC Drug Label
Date: 20250107

ACTIVE INGREDIENTS: LOPERAMIDE HYDROCHLORIDE 2 mg/1 1; DIMETHICONE 125 mg/1 1
INACTIVE INGREDIENTS: ACESULFAME POTASSIUM; CROSCARMELLOSE SODIUM; ANHYDROUS DIBASIC CALCIUM PHOSPHATE; MICROCRYSTALLINE CELLULOSE 101; MICROCRYSTALLINE CELLULOSE 102; STEARIC ACID

Drug Facts

Active ingredients (in each caplet)

Loperamide HCl USP 2 mg
Simethicone USP 125 mg

Purposes

Anti-diarrheal
Anti-gas

Uses

relieves symptoms of diarrhea plus bloating, pressure and cramps, commonly referred to as gas

Warnings

Allergy alert: Do not use if you have ever had a rash or other allergic reaction to loperamide HCl

Heart alert: Taking more than directed can cause serious heart problems or death

Do not use

- if you have bloody or black stool
- if you have difficulty swallowing

Ask a doctor before use if you have

- fever
- mucus in the stool
- a history of liver disease
- a history of abnormal heart rhythm

Ask a doctor or pharmacist before use if you are

taking a prescription drug. Loperamide may interact with certain prescription drugs.

When using this product

tiredness, drowsiness or dizziness may occur. Be careful when driving or operating machinery.

Stop use and ask a doctor if

- symptoms get worse
- diarrhea lasts for more than 2 days
- you get abdominal swelling or bulging. These may be signs of a serious condition.
- you have difficulty swallowing the caplet

If pregnant or breast-feeding,

ask a health professional before use.

Keep out of reach of children.

In case of overdose, get medical help or contact a Poison Control Center right away.

(1-800-222-1222)

Directions

- drink plenty of clear fluids to help prevent dehydration caused by diarrhea
- take only on an empty stomach (1 hour before or 2 hours after a meal)
- take with a full (8 oz.) glass of water
- find right dose on chart below. If possible, use weight to dose; otherwise, use age.

adults and children 12 years and over | 2 caplets after the first loose stool; 1 caplet after each subsequent loose stool; but no more than 4 caplets in 24 hours
children 9 to 11 years (60 to 95 lbs) | 1 caplet after the first loose stool; ½ caplet after each subsequent loose stool; but no more than 3 caplets in 24 hours
children 6 to 8 years (48 to 59 lbs) | 1 caplet after the first loose stool; ½ caplet after each subsequent loose stool; but no more than 2 caplets in 24 hours
children 2 to 5 years (34 to 47 lbs) | ask a doctor
children under 2 years (up to 33 lbs) | do not use

Other information

- each caplet contains: calcium 165 mg, sodium 4 mg
- store between 20° to 25°C (68° to 77°F). Protect from light.
- do not use if carton is opened or if individual blister units are torn or opened

Inactive ingredients

acesulfame potassium, croscarmellose sodium, dibasic calcium phosphate anhydrous, flavor, microcrystalline cellulose, stearic acid.

Questions or comments?

call 1-855-274-4122

(Monday – Friday 8:30 AM to 5:00 PM EST)

Distributed by:
AUROHEALTH LLC
279 Princeton-Hightstown Road
East Windsor, NJ 08520
Made in India
Code: AP/DRUGS/04/2016

PACKAGE LABEL-PRINCIPAL DISPLAY PANEL - 2 mg/125mg (24 Caplets) Blister Carton Label

NDC 58602-869-76
PrimaryHealth
** COMPARE TO Imodium®
Multi-Sympton Relief active ingredients

Loperamide HCl and Simethicone Tablets
2 mg/125 mg
Multi-Sympton Relief
Caplet
Loperamide HCl 2 mg - Antidiarrheal
Simethicone 125 mg - Anti-gas
Relieves symptoms of diarrhea plus

• Cramps & Pressure
• Bloating
• Gas

Actual Size
24 Caplets*
*capsule-shaped tablets